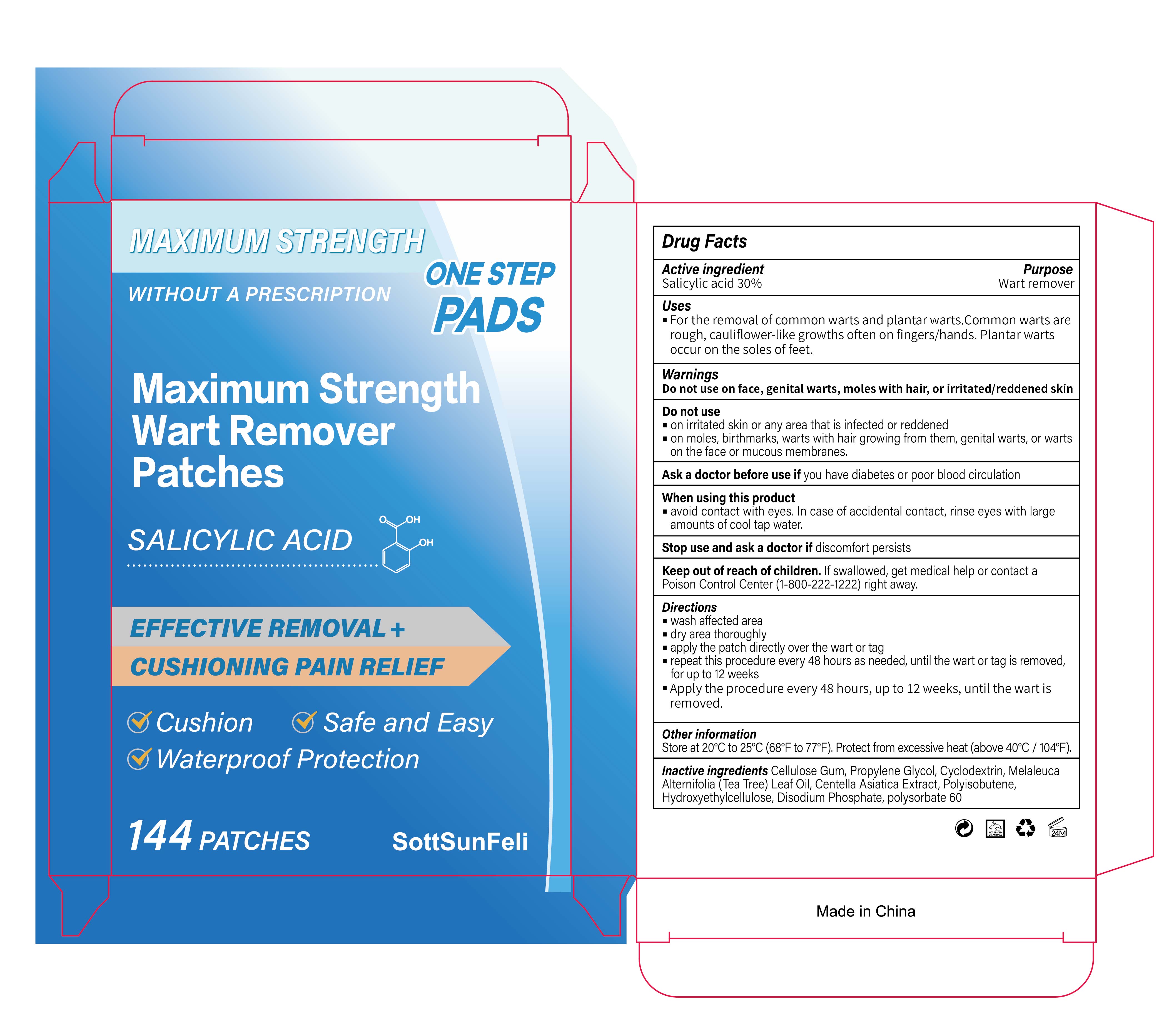 DRUG LABEL: Maximum Strength Wart Remover Patches
NDC: 85136-011 | Form: PATCH
Manufacturer: Henan Toudaorong Biotechnology Co., Ltd.
Category: otc | Type: HUMAN OTC DRUG LABEL
Date: 20251123

ACTIVE INGREDIENTS: SALICYLIC ACID 30 mg/100 mg
INACTIVE INGREDIENTS: POLYSORBATE 60; PROPYLENE GLYCOL; HYDROXYETHYL CELLULOSE (140 CPS AT 5%); CELLULOSE GUM; CENTELLA ASIATICA; DISODIUM PHOSPHATE; CYCLODEXTRIN; MELALEUCA ALTERNIFOLIA (TEA TREE) LEAF OIL; POLYISOBUTYLENE (1000 MW)

Active ingredient

Salicylic acid 30%
Purpose Wart remove

Keep out of reach of children. lf swallowed, get medical help or contact aPoison Control Center (1-800-222-1222)right away.

PURPOSE

For the removal of common warts and plantar warts.Common warts arerough, cauliflower-like growths often on fingers/hands. Plantar wartsoccur on the soles of feet.

Warnings

Do not use on face, genital warts, moles with hair, or irritated/reddened skin

INACTIVE INGREDIENT

Inactive ingredients Cellulose Gum, Propylene Glycol, Cyclodextrin, MelaleucaAlternifolia (Tea Tree) Leaf Oil, Centella Asiatica Extract, Polvisobutene.Hvdroxvethylcelulose,Disodium Phosphate, polysorbate 60
0图

INDICATIONS AND USAGE

on irritated skin or any area that is infected or reddened"

on moles, birthmarks, warts with hair growing from them, genital warts, or wartson the face or mucous membranes,

Directions

wash afected areadry area thoroughly apply the patch directly over the wart or tagrepeat this procedure every 48 hours as needed, until the wart or tag is removedf崧or up to 12 weeks"Apply the procedure every 48 hours, up to 12 weeks, until the wart isremoved.